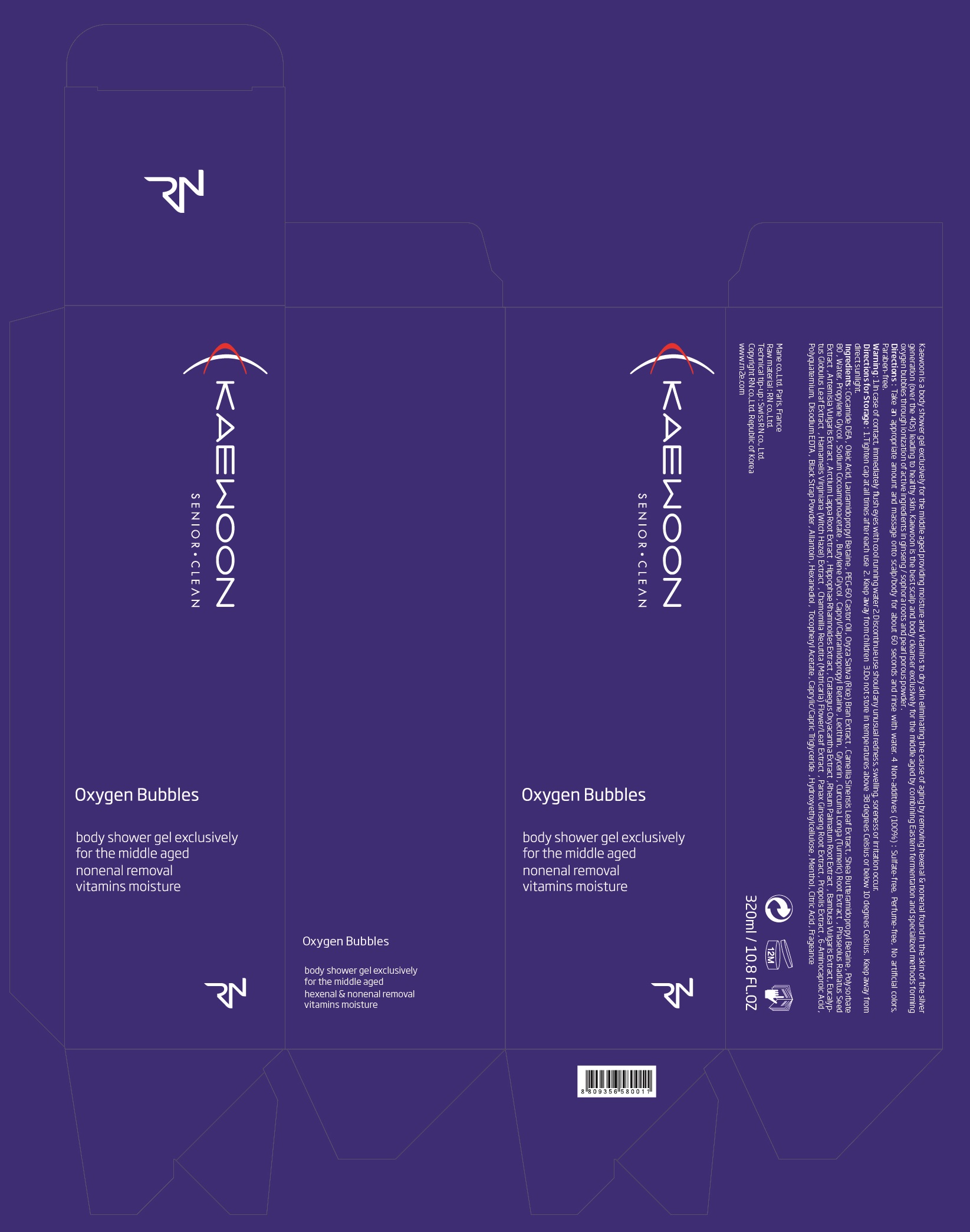 DRUG LABEL: KAEWOON
NDC: 71237-001 | Form: GEL
Manufacturer: RNCARE
Category: otc | Type: HUMAN OTC DRUG LABEL
Date: 20211004

ACTIVE INGREDIENTS: ALLANTOIN 2 mg/1 mL; GLYCERIN 30 mg/1 mL
INACTIVE INGREDIENTS: COCO DIETHANOLAMIDE; OLEIC ACID; LAURAMIDOPROPYL BETAINE; PEG-60 CASTOR OIL; RICE BRAN; GREEN TEA LEAF; POLYSORBATE 80; WATER; PROPYLENE GLYCOL; SODIUM COCOAMPHOACETATE; BUTYLENE GLYCOL; EGG PHOSPHOLIPIDS; TURMERIC; MUNG BEAN; ARTEMISIA VULGARIS ROOT; ARCTIUM LAPPA ROOT; HIPPOPHAE RHAMNOIDES FRUIT; CRATAEGUS LAEVIGATA FLOWER; RHEUM PALMATUM ROOT; BAMBUSA VULGARIS TOP; EUCALYPTUS GLOBULUS LEAF; HAMAMELIS VIRGINIANA TOP; MATRICARIA RECUTITA FLOWERING TOP; ASIAN GINSENG; PROPOLIS WAX; AMINOCAPROIC ACID; EDETATE DISODIUM; HEXANEDIOL; .ALPHA.-TOCOPHEROL ACETATE; MEDIUM-CHAIN TRIGLYCERIDES; HYDROXYETHYL CELLULOSE (100 MPA.S AT 2%); MENTHOL, UNSPECIFIED FORM; CITRIC ACID MONOHYDRATE

71237-001_V3

ACTIVE INGREDIENT

Glycerin 3%

Allantoin 0.2%

PURPOSE

Skin Protectant

INDICATIONS AND USAGE

Body Cleansing

DOSAGE AND ADMINISTRATION

Take an appropriate amount and massage onto scalp/body for about 60 seconds and rinse with water

WARNINGS

In case of eye contact, immediately rinse with water

Stop use if unusual redness, swelling, soreness or irritation occur

Keep out of reach of children

INACTIVE INGREDIENT

Cocamide DEA, Oleic Acid, Lauramidopropyl Betaine, PEG-60 Castor Oil, Oryza Sativa (Rice) Bran Extract, Camellia Sinensis Leaf Extract, Shea Butteramidopropyl Betaine, Polysorbate 80, Water, Propylene Glycol, Sodium Cocoamphoacetate, Butylene Glycol, Capryl/Capramidopropyl Betaine, Lecithin, Curcuma Longa (Turmeric) Root Extract, Phaseolus Radiatus Seed Extract, Artemisia Vulgaris Extract, Arctium Lappa Root Extract, Hippophae Rhamnoides Extract, Crataegus Oxyacantha Extract, Rheum Palmatum Root Extract, Bambusa Vulgaris Extract, Eucalyptus Globulus Leaf Extract, Hamamelis Virginiana (Witch Hazel) Extract, Chamomilla Recutita (Matricaria) Flower/Leaf Extract, Panax Ginseng Root Extract, Propolis Extract, 6-Aminocaproic Acid, Polyquaternium, Disodium EDTA, Black Strap Powder, Hexanediol, Tocopheryl Acetate, Caprylic/Capric Triglyceride, Hydroxyethylcellulose, Menthol, Citric Acid, Frageance